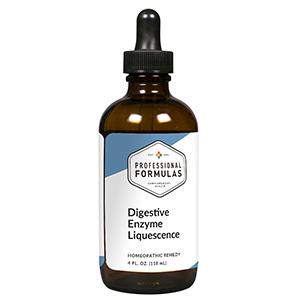 DRUG LABEL: Digestive Enzyme Liquescence
NDC: 63083-3007 | Form: LIQUID
Manufacturer: Professional Complementary Health Formulas
Category: homeopathic | Type: HUMAN OTC DRUG LABEL
Date: 20190815

ACTIVE INGREDIENTS: CORIANDER OIL 2 [hp_X]/118 mL; BERBERIS VULGARIS ROOT BARK 3 [hp_X]/118 mL; BROMELAINS 3 [hp_X]/118 mL; ARTEMISIA ANNUA FLOWERING TOP 3 [hp_X]/118 mL; CINNAMON 3 [hp_X]/118 mL; GENTIANA LUTEA ROOT 3 [hp_X]/118 mL; STAR ANISE 3 [hp_X]/118 mL; MARRUBIUM VULGARE WHOLE 3 [hp_X]/118 mL; PAPAIN 3 [hp_X]/118 mL; SYZYGIUM CUMINI SEED 3 [hp_X]/118 mL; GINGER 3 [hp_X]/118 mL; GOLDENSEAL 5 [hp_X]/118 mL; BOS TAURUS BILE 6 [hp_X]/118 mL; BOS TAURUS GALLBLADDER 6 [hp_X]/118 mL; BEEF LIVER 6 [hp_X]/118 mL; BOS TAURUS PANCREAS 6 [hp_X]/118 mL; PANCRELIPASE AMYLASE 6 [hp_X]/118 mL; HISTATIN 3 6 [hp_X]/118 mL; TRIPE 6 [hp_X]/118 mL
INACTIVE INGREDIENTS: ALCOHOL; WATER

T7

ACTIVE INGREDIENTS

Coriandrum sativum 2X
Berberis vulgaris 3X
Bromelain 3X
Chamomilla 3X
Cinnamomum 3X
Gentiana lutea 3X
Illicium anisatum 3X
Marrubium vulgare 3X
Papain 3X
Syzygium jambolanum 3X
Zingiber officinale 3X
Hydrastis canadensis 5X
Fel tauri 6X
Gallbladder 6X
Liver 6X
Pancreas 6X
Pancreatinum 6X
Parotid 6X
Stomach 6X

QUESTIONS

Professional Formulas

PO Box 2034 Lake Oswego, OR 97035

INDICATIONS

For the temporary relief of minor abdominal pain or cramps, gas or bloating, mild constipation, heartburn, or periodic nausea.*

PURPOSE

*Claims based on traditional homeopathic practice, not accepted medical evidence. Not FDA evaluated.

WARNINGS

In case of overdose, get medical help or contact a poison control center right away.

Keep out of the reach of children.

PREGNANCY OR BREAST FEEDING

If pregnant or breastfeeding, ask a healthcare professional before use.

DIRECTIONS

Place drops under tongue 30 minutes before/after meals. Adults and children 12 years and over: Take one full dropper up to 2 times per day. Consult a physician for use in children under 12 years of age.

OTHER INFORMATION

Tamper resistant. If seal is broken, do not use. After opening, close container tightly and store at room temperature away from heat.

INACTIVE INGREDIENTS

20% ethanol, purified water.

LABEL

Est 1985

Professional Formulas

Complementary Health

Digestive Enzyme Liquescence

Homeopathic Remedy

4 FL. OZ. (118 mL)